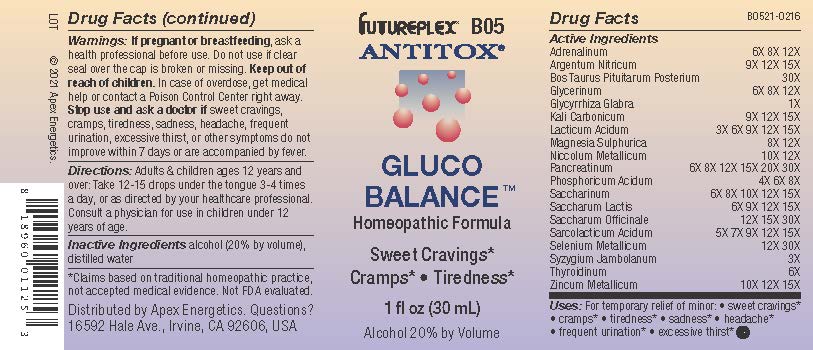 DRUG LABEL: B05
NDC: 63479-0205 | Form: SOLUTION/ DROPS
Manufacturer: Apex Energetics Inc.
Category: homeopathic | Type: HUMAN OTC DRUG LABEL
Date: 20240108

ACTIVE INGREDIENTS: POTASSIUM CARBONATE 15 [hp_X]/1 mL; NICKEL 12 [hp_X]/1 mL; PHOSPHORIC ACID 8 [hp_X]/1 mL; LACTIC ACID, L- 15 [hp_X]/1 mL; SILVER NITRATE 15 [hp_X]/1 mL; GLYCERIN 12 [hp_X]/1 mL; GLYCYRRHIZA GLABRA 1 [hp_X]/1 mL; LACTOSE, UNSPECIFIED FORM 15 [hp_X]/1 mL; SUCROSE 30 [hp_X]/1 mL; SELENIUM 30 [hp_X]/1 mL; MAGNESIUM SULFATE HEPTAHYDRATE 12 [hp_X]/1 mL; PANCRELIPASE 30 [hp_X]/1 mL; SYZYGIUM CUMINI SEED 3 [hp_X]/1 mL; ZINC 15 [hp_X]/1 mL; LACTIC ACID, DL- 15 [hp_X]/1 mL; SACCHARIN 15 [hp_X]/1 mL; THYROID, UNSPECIFIED 6 [hp_X]/1 mL; EPINEPHRINE 12 [hp_X]/1 mL; BOS TAURUS PITUITARY GLAND, POSTERIOR 30 [hp_X]/1 mL
INACTIVE INGREDIENTS: ALCOHOL; WATER

B05

Active Ingredients
Adrenalinum | 6X 8X 12X
Argentum Nitricum | 9X 12X 15X
Bos Taurus Pituitarum Posterium | 30X
Glycerinum | 6X 8X 12X
Glycyrrhiza Glabra | 1X
Kali Carbonicum | 9X 12X 15X
Lacticum Acidum | 3X 6X 9X 12X 15X
Magnesia Sulphurica | 8X 12X
Niccolum Metallicum | 10X 12X
Pancreatinum | 6X 8X 12X 15X 20X 30X
Phosphoricum Acidum | 4X 6X 8X
Saccharinum | 6X 8X 10X 12X 15X
Saccharum Lactis | 6X 9X 12X 15X
Saccharum Officinale | 12X 15X 30X
Sarcolacticum Acidum | 5X 7X 9X 12X 15X
Selenium Metallicum | 12X 30X
Syzygium Jambolanum | 3X
Thyroidinum | 6X

INDICATIONS AND USAGE

Uses:

For temporary relief of minor:

sweet cravings*

cramps*

tiredness*

sadness*

headache*

frequent urination*

excessive thirst*

*Claims based on traditional homeopathic practice, not accepted medical evidence. Not FDA evaluated.

WARNINGS

PREGNANCY OR BREAST FEEDING

If pregnant or breastfeeding, ask a health professional before use.

Do not use if clear seal over the cap is broken or missing.

Keep out of reach of children. In case of overdose, get medical help or contact a Poison Control Center right away.

Stop use and ask a doctor if sweet cravings, cramps, tiredness, sadness, headache, frequent urination, excessive thirst, or other symptoms do not improve within 7 days or are accompanied by fever.

Directions:

Adults & children ages 12 years and over: Take 12-15 drops under the tongue 3-4 times a day, or as directed by your healthcare professional. Consult a physician for use in children under 12 years of age.

Inactive Ingredients

alcohol (20% by volume), distilled water

Distributed by Apex Energetics. Questions?

16592 Hale Ave., Irvine, CA 92606, USA

PACKAGE LABEL

UREPLEX® B05

ANTITOX®

GLUCO BALANCE™

Homeopathic Formula

Sweet Cravings*

Cramps*

Tiredness*

1 fl oz (30 mL)

Alcohol 20% by Volume